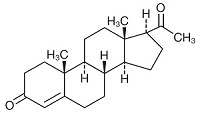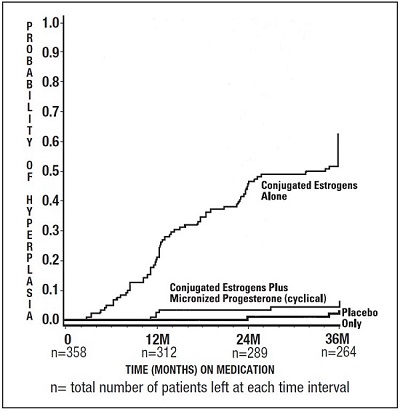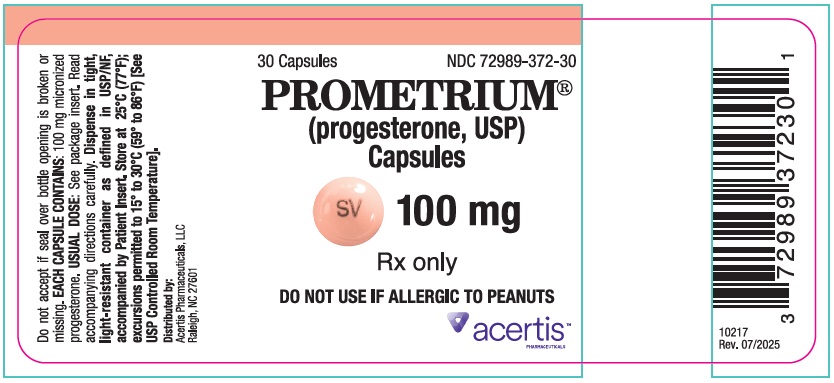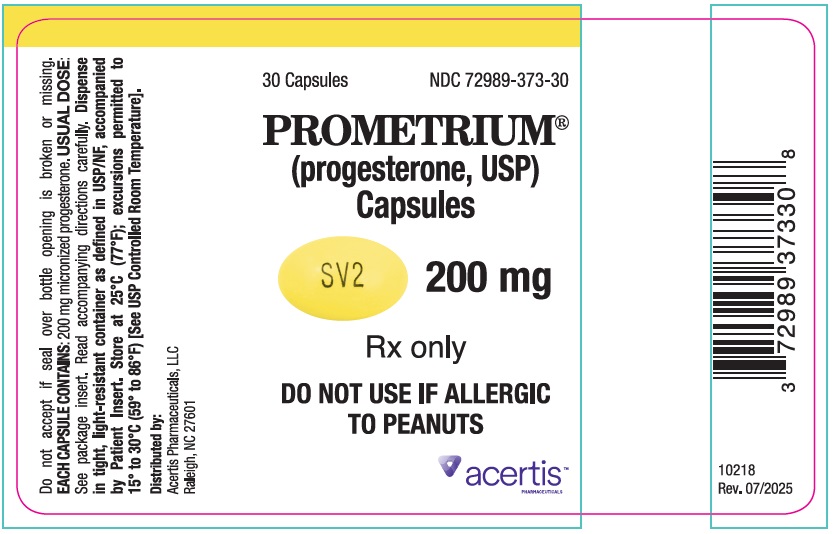 DRUG LABEL: Prometrium
NDC: 72989-372 | Form: CAPSULE
Manufacturer: Acertis Pharmaceuticals, LLC
Category: prescription | Type: HUMAN PRESCRIPTION DRUG LABEL
Date: 20260106

ACTIVE INGREDIENTS: PROGESTERONE 100 mg/1 1
INACTIVE INGREDIENTS: PEANUT OIL; GELATIN, UNSPECIFIED; GLYCERIN; LECITHIN, SOYBEAN; TITANIUM DIOXIDE; FD&C RED NO. 40; D&C YELLOW NO. 10

PROMETRIUM®
(progesterone, USP)

Capsules 100 mg

Capsules 200 mg

Rx only

DESCRIPTION

PROMETRIUM® (progesterone, USP) Capsules contain micronized progesterone for oral administration. Progesterone has a molecular weight of 314.47 and a molecular formula of C21H30O2. Progesterone (pregn-4-ene-3, 20-dione) is a white or creamy white, odorless, crystalline powder practically insoluble in water, soluble in alcohol, acetone and dioxane and sparingly soluble in vegetable oils, stable in air, melting between 126° and 131°C. The structural formula is:

Progesterone is synthesized from a starting material from a plant source and is chemically identical to progesterone of human ovarian origin. PROMETRIUM Capsules are available in multiple strengths to afford dosage flexibility for optimum management. PROMETRIUM Capsules contain 100 mg or 200 mg micronized progesterone.

The inactive ingredients for PROMETRIUM Capsules 100 mg include: peanut oil NF, gelatin NF, glycerin USP, lecithin NF, titanium dioxide USP, FD&C Red No. 40, and D&C Yellow No. 10.

The inactive ingredients for PROMETRIUM Capsules 200 mg include: peanut oil NF, gelatin NF, glycerin USP, lecithin NF, titanium dioxide USP, D&C Yellow No. 10, and FD&C Yellow No. 6.

CLINICAL PHARMACOLOGY

PROMETRIUM Capsules are an oral dosage form of micronized progesterone which is chemically identical to progesterone of ovarian origin. The oral bioavailability of progesterone is increased through micronization.

Pharmacokinetics

A. Absorption

After oral administration of progesterone as a micronized soft-gelatin capsule formulation, maximum serum concentrations were attained within 3 hours. The absolute bioavailability of micronized progesterone is not known. Table 1 summarizes the mean pharmacokinetic parameters in postmenopausal women after five oral daily doses of PROMETRIUM Capsules 100 mg as a micronized soft-gelatin capsule formulation.

TABLE 1. Pharmacokinetic Parameters of PROMETRIUM Capsules
Parameter | PROMETRIUM Capsules Daily Dose
Parameter | 100 mg | 200 mg | 300 mg
Cmax (ng/mL) | 17.3 ± 21.9 [Mean ± S.D.] | 38.1 ± 37.8 | 60.6 ± 72.5
Tmax (hr) | 1.5 ± 0.8 | 2.3 ± 1.4 | 1.7 ± 0.6
AUC (0-10) (ng × hr/mL) | 43.3 ± 30.8 | 101.2 ± 66.0 | 175.7 ± 170.3

Serum progesterone concentrations appeared linear and dose proportional following multiple dose administration of PROMETRIUM® (progesterone, USP) Capsules 100 mg over the dose range 100 mg per day to 300 mg per day in postmenopausal women. Although doses greater than 300 mg per day were not studied in females, serum concentrations from a study in male volunteers appeared linear and dose proportional between 100 mg per day and 400 mg per day. The pharmacokinetic parameters in male volunteers were generally consistent with those seen in postmenopausal women.

B. Distribution

Progesterone is approximately 96 percent to 99 percent bound to serum proteins, primarily to serum albumin (50 to 54 percent) and transcortin (43 to 48 percent).

C. Metabolism

Progesterone is metabolized primarily by the liver largely to pregnanediols and pregnanolones. Pregnanediols and pregnanolones are conjugated in the liver to glucuronide and sulfate metabolites. Progesterone metabolites which are excreted in the bile may be deconjugated and may be further metabolized in the intestine via reduction, dehydroxylation, and epimerization.

D. Excretion

The glucuronide and sulfate conjugates of pregnanediol and pregnanolone are excreted in the bile and urine. Progesterone metabolites are eliminated mainly by the kidneys. Progesterone metabolites which are excreted in the bile may undergo enterohepatic recycling or may be excreted in the feces.

E. Special Populations

The pharmacokinetics of PROMETRIUM Capsules have not been assessed in low body weight or obese patients.

Hepatic Insufficiency: The effect of hepatic impairment on the pharmacokinetics of PROMETRIUM Capsules has not been studied.

Renal Insufficiency: The effect of renal impairment on the pharmacokinetics of PROMETRIUM Capsules has not been studied.

F. Food–Drug Interaction

Concomitant food ingestion increased the bioavailability of PROMETRIUM Capsules relative to a fasting state when administered to postmenopausal women at a dose of 200 mg.

G. Drug Interactions

The metabolism of progesterone by human liver microsomes was inhibited by ketoconazole (IC50 < 0.1 μM). Ketoconazole is a known inhibitor of cytochrome P450 3A4, hence these data suggest that ketoconazole or other known inhibitors of this enzyme may increase the bioavailability of progesterone. The clinical relevance of the in vitro findings is unknown.

Coadministration of conjugated estrogens and PROMETRIUM Capsules to 29 postmenopausal women over a 12-day period resulted in an increase in total estrone concentrations (Cmax 3.68 ng/mL to 4.93 ng/mL) and total equilin concentrations (Cmax 2.27 ng/mL to 3.22 ng/mL) and a decrease in circulating 17β estradiol concentrations (Cmax 0.037 ng/mL to 0.030 ng/mL). The half-life of the conjugated estrogens was similar with coadministration of PROMETRIUM Capsules. Table 2 summarizes the pharmacokinetic parameters.

TABLE 2. Mean (± S.D.) Pharmacokinetic Parameters for Estradiol, Estrone, and Equilin Following Coadministration of Conjugated Estrogens 0.625 mg and PROMETRIUM Capsules 200 mg for 12 Days to Postmenopausal Women
 | Conjugated Estrogens |  |  | Conjugated Estrogens plus PROMETRIUM Capsules
Drug | Cmax (ng/mL) | Tmax (hr) | AUC(0-24h) (ng × h/mL) | Cmax (ng/mL) | Tmax (hr) | AUC(0-24h) (ng × h/mL)
Estradiol | 0.037 ± 0.048 | 12.7 ± 9.1 | 0.676 ± 0.737 | 0.030 ± 0.032 | 17.32 ± 1.21 | 0.561 ± 0.572
Estrone Total [Total estrogens is the sum of conjugated and unconjugated estrogen.] | 3.68 ± 1.55 | 10.6 ± 6.8 | 61.3 ± 26.36 | 4.93 ± 2.07 | 7.5 ± 3.8 | 85.9 ± 41.2
Equilin Total | 2.27 ± 0.95 | 6.0 ± 4.0 | 28.8 ± 13.0 | 3.22 ± 1.13 | 5.3 ± 2.6 | 38.1 ± 20.2

CLINICAL STUDIES

Effects on the endometrium

In a randomized, double-blind clinical trial, 358 postmenopausal women, each with an intact uterus, received treatment for up to 36 months. The treatment groups were: PROMETRIUM® (progesterone, USP) Capsules at the dose of 200 mg per day for 12 days per 28-day cycle in combination with conjugated estrogens 0.625 mg per day (n=120); conjugated estrogens 0.625 mg per day only (n=119); or placebo (n=119). The subjects in all three treatment groups were primarily Caucasian women (87 percent or more of each group). The results for the incidence of endometrial hyperplasia in women receiving up to 3 years of treatment are shown in Table 3. A comparison of the PROMETRIUM Capsules plus conjugated estrogens treatment group to the conjugated estrogens only group showed a significantly lower rate of hyperplasia (6 percent combination product versus 64 percent estrogen alone) in the PROMETRIUM Capsules plus conjugated estrogens treatment group throughout 36 months of treatment.

TABLE 3. Incidence of Endometrial Hyperplasia in Women Receiving 3 Years of Treatment
Endometrial Diagnosis | Treatment Group
 | Conjugated Estrogens 0.625 mg + PROMETRIUM Capsules 200 mg (cyclical) |  | Conjugated Estrogens 0.625 mg (alone) |  | Placebo
 | Number of patients | % of patients | Number of patients | % of patients | Number of patients | % of patients
 | n=117 |  | n=115 |  | n=116
HYPERPLASIA [Most advanced result to least advanced result: Adenocarcinoma > atypical hyperplasia > complex hyperplasia > simple hyperplasia] | 7 | 6 | 74 | 64 | 3 | 3
Adenocarcinoma | 0 | 0 | 0 | 0 | 1 | 1
Atypical hyperplasia | 1 | 1 | 14 | 12 | 0 | 0
Complex hyperplasia | 0 | 0 | 27 | 23 | 1 | 1
Simple hyperplasia | 6 | 5 | 33 | 29 | 1 | 1

The times to diagnosis of endometrial hyperplasia over 36 months of treatment are shown in Figure 1. This figure illustrates graphically that the proportion of patients with hyperplasia was significantly greater for the conjugated estrogens group (64 percent) compared to the conjugated estrogens plus PROMETRIUM Capsules group (6 percent).

Figure 1. Time to Hyperplasia in Women Receiving up to 36 Months of Treatment

The discontinuation rates due to hyperplasia over the 36 months of treatment are as shown in Table 4. For any degree of hyperplasia, the discontinuation rate for patients who received conjugated estrogens plus PROMETRIUM Capsules was similar to that of the placebo only group, while the discontinuation rate for patients who received conjugated estrogens alone was significantly higher. Women who permanently discontinued treatment due to hyperplasia were similar in demographics to the overall study population.

TABLE 4. Discontinuation Rate Due to Hyperplasia Over 36 Months of Treatment
Most Advanced Biopsy Result Through 36 Months of Treatment | Treatment Group
 | Conjugated Estrogens + PROMETRIUM Capsules (cyclical) |  | Conjugated Estrogens (alone) |  | Placebo
 | n=120 |  | n=119 |  | n=119
 | Number of patients | % of patients | Number of patients | % of patients | Number of patients | % of patients
Adenocarcinoma | 0 | 0 | 0 | 0 | 1 | 1
Atypical hyperplasia | 1 | 1 | 10 | 8 | 0 | 0
Complex hyperplasia | 0 | 0 | 21 | 18 | 1 | 1
Simple hyperplasia | 1 | 1 | 13 | 11 | 0 | 0

Effects on secondary amenorrhea

In a single-center, randomized, double-blind clinical study that included premenopausal women with secondary amenorrhea for at least 90 days, administration of 10 days of PROMETRIUM® (progesterone, USP) Capsules therapy resulted in 80 percent of women experiencing withdrawal bleeding within 7 days of the last dose of PROMETRIUM Capsules, 300 mg per day (n=20), compared to 10 percent of women experiencing withdrawal bleeding in the placebo group (n=21).

In a multicenter, parallel-group, open label, postmarketing dosing study that included premenopausal women with secondary amenorrhea for at least 90 days, administration of 10 days of PROMETRIUM Capsules during two 28-day treatment cycles, 300 mg per day (n=107) or 400 mg per day (n=99), resulted in 73.8 percent and 76.8 percent of women, respectively, experiencing withdrawal bleeding.

The rate of secretory transformation was evaluated in a multicenter, randomized, double-blind clinical study in estrogen-primed postmenopausal women. PROMETRIUM Capsules administered orally for 10 days at 400 mg per day (n=22) induced complete secretory changes in the endometrium in 45 percent of women compared to 0 percent in the placebo group (n=23).

A second multicenter, parallel-group, open label postmarketing dosing study in premenopausal women with secondary amenorrhea for at least 90 days also evaluated the rate of secretory transformation. All subjects received daily oral conjugated estrogens over 3 consecutive 28-day treatment cycles and PROMETRIUM Capsules, 300 mg per day (n=107) or 400 mg per day (n=99) for 10 days of each treatment cycle. The rate of complete secretory transformation was 21.5 percent and 28.3 percent, respectively.

Women's Health Initiative Estrogen Plus Progestin Trial

The WHI estrogen plus progestin trial enrolled predominantly healthy postmenopausal women to assess the risks and benefits of daily oral CE (0.625 mg) in combination with MPA (2.5 mg) compared to placebo in the prevention of certain chronic diseases. The primary endpoint was the incidence of CHD (defined as nonfatal MI, silent MI and CHD death), with invasive breast cancer as the primary adverse outcome. A "global index" included the earliest occurrence of CHD, invasive breast cancer, stroke, PE, endometrial cancer colorectal cancer, hip fracture, or death due to other causes. This trial did not evaluate the effects of CE plus MPA on menopausal symptoms.

The WHI estrogen plus progestin trial was stopped early. After an average follow-up of 5.6 years of treatment, the increased risk of invasive breast cancer crossed the predefined stopping threshold. The global index was supportive of a finding of overall harm. The absolute excess risk of events included in the global index was 19 per 10,000 women-years.
Results of the trial, which enrolled 16,608 women (average 63 years of age, range 50 to 79; 83.9%White, 6.8% Black, 5.4% Hispanic, 3.9% Other) are presented in Table 5. These results reflect centrally adjudicated data after an average follow-up of 5.6 years.

TABLE 5. Relative and Absolute Risk Seen in the WHI Estrogen Plus Progestin Trial at an Average of 5.6 Years [Adapted from numerous WHI publications. WHI publications can be viewed at www.nhlbi.nih.gov/whi.] , [Results are based on centrally adjudicated data.]
Event | Relative Ratio (95% CI) [Nominal confidence intervals unadjusted for multiple looks and multiple comparisons.] | Risk Difference (CE/MPA vs placebo/10,000 WYs)
Event | Relative Ratio (95% CI) [Nominal confidence intervals unadjusted for multiple looks and multiple comparisons.] | CHD events Non-fatal MI CHD death | 1.18 (0.95-1.45) 1.24 (0.98-1.56) 1.05 (0.76-1.45) | 6 (41 vs 35) 6 (35 vs 29) 1 (16 vs 15)
All Strokes | 1.37 (1.07-1.76) | 9 (33 vs 24)
Deep vein thrombosis [Not included in Global Index.] | 1.87 (1.37-2.54) | 12 (25 vs 14)
Pulmonary embolism | 1.98 (1.36-2.87) | 9 (18 vs 9)
Invasive breast cancer [Includes metastatic and non-metastatic breast cancer with the exception of in situ breast cancer.] | 1.24 (1.01-1.53) | 9 (43 vs 35)
Colorectal cancer | 0.62 (0.43-0.89) | -6 (10 vs 17)
Endometrial cancer | 0.83 (0.49-1.40) | -1 (6 vs 7)
Hip fracture | 0.67 (0.47-0.95) | -6 (11 vs 17)
Vertebral fractures | 0.68 (0.48-0.96) | -6 (12 vs 17)
Total fractures | 0.76 (0.69-0.83) | -51 (161 vs 212)
Overall mortality, [All deaths, except from breast or colorectal cancer, definite or probable CHD, PE or cerebrovascular disease.] | 0.97 (0.81-1.16) | -1 (52 vs 53)
Global Index [A subset of the events was combined in a "global index" defined as the earliest occurrence of CHD events, invasive breast cancer, stroke, pulmonary embolism, endometrial cancer, colorectal cancer, hip fracture, or death due to other causes.] | 1.12 (1.02-1.24) | 20 (189 vs 168)

Timing of the initiation of estrogen plus progestin therapy relative to the start of menopause may affect the overall risk benefit profile. The results of the WHI estrogen plus progestin trial in women 50 to 59 years of age (N=2,837 for CE/MPA; N=2,683 for placebo) are shown in Table 6.

Table 6. Relative Risk and Risk Difference Observed Among Women 50-59 Years of Age in the WHI Estrogen Plus Progestin Trial at an Average of 5.6 [Adapted from 2013 WHI trial (CE/MPA n=2,837; placebo=2,683). WHI publications can be viewed at www.nhlbi.nih.gov/whi.] , [Results are based on centrally adjudicated data.]
Event | Relative Ratio (95% CI) [In the WHI studies, hazard ratios were estimated using Cox proportional hazards models comparing treatment to placebo; however, they are described here as relative risks. Nominal confidence intervals unadjusted for multiple looks and multiple comparisons.] | Risk Difference (CE/MPA vs placebo/10,000 WYs)
Event | Relative Ratio (95% CI) [In the WHI studies, hazard ratios were estimated using Cox proportional hazards models comparing treatment to placebo; however, they are described here as relative risks. Nominal confidence intervals unadjusted for multiple looks and multiple comparisons.] | CHD events Non-fatal MI CHD death | 1.34 (0.82-2.19) 1.32 (0.77-2.25) 0.77 (0.33-1.79) | 5 (23 vs 17) 4 (19 vs 15) -2 (6 vs 8)
All Strokes | 1.51 (0.81-2.82) | 5 (15 vs 10)
Deep vein thrombosis [Not included in “global index.”] | 3.01 (1.36-6.66) | 10 (15 vs 5)
Pulmonary embolism | 2.05 (0.89-4.71) | 6 (11 vs 5)
Invasive breast cancer [Includes metastatic and non-metastatic breast cancer with the exception of in situ cancer.] | 1.21 (0.81-1.80) | 6 (33 vs 27)
Colorectal cancer | 0.79 (0.29-2.18) | -1 (4 vs 5)
Endometrial cancer | 1.07 (0.33-3.53) | 0 (4 vs 3)
Hip fracture | 0.17 (0.22-1.45) | -3 (1 vs 3)
Vertebral fractures | 0.38 (0.15-0.97) | -6 (4 vs 10)
Total fractures | 0.82 (0.68-1.00) | -25 (120 vs 145)
Overall mortality, [All deaths, except from breast or colorectal cancer, definite or probable CHD, PE or cerebrovascular disease.] | 0.67 (0.43-1.04) | -10 (21 vs 31)
Global Index [A subset of the events was combined in a “global index,” defined as the earliest occurrence of CHD events, invasive breast cancer, stroke, PE, colorectal cancer, hip fracture, or death due to other causes.] | 1.12 (0.89-1.40) | 12 (103 vs 91)

Women's Health Initiative Memory Study

The estrogen plus progestin Women's Health Initiative Memory Study (WHIMS), an ancillary study of WHI, enrolled 4,532 predominantly healthy postmenopausal women 65 years of age and older (47 percent were 65 to 69 years of age; 35 percent were 70 to 74 years of age; and 18 percent were 75 years of age and older) to evaluate the effects of daily CE (0.625 mg) plus MPA (2.5 mg) on the incidence of probable dementia (primary outcome) compared to placebo.

After an average follow-up of 4 years, the relative risk of probable dementia for CE plus MPA versus placebo was 2.05 (95 percent CI, 1.21 – 3.48). The absolute risk of probable dementia for CE plus MPA versus placebo was 45 versus 22 per 10,000 women-years. Probable dementia as defined in this study included Alzheimer's disease (AD), vascular dementia (VaD) and mixed type (having features of both AD and VaD). The most common classification of probable dementia in the treatment group and the placebo group was AD. Since the ancillary study was conducted in women 65 to 79 years of age, it is unknown whether these findings apply to younger postmenopausal women. (See PRECAUTIONS, Geriatric Use.)

INDICATIONS AND USAGE

PROMETRIUM® (progesterone, USP) Capsules are indicated for use in the prevention of endometrial hyperplasia in nonhysterectomized postmenopausal women who are receiving conjugated estrogens tablets. They are also indicated for use in secondary amenorrhea.

CONTRAINDICATIONS

PROMETRIUM is contraindicated in women with any of the following conditions:

1. Hypersensitivity to its ingredients. PROMETRIUM Capsules contain peanut oil and is contraindicated in patients allergic to peanuts.
2. Abnormal genital bleeding of unknown etiology.
3. Known, suspected, or history of breast cancer.
4. Active deep vein thrombosis, pulmonary embolism or history of these conditions.
5. Active arterial thromboembolic disease (for example, stroke and myocardial infarction), or a history of these conditions.
6. Known liver dysfunction or disease.

WARNINGS

1. Cardiovascular disorders

PROMETRIUM is contraindicated in females with active DVT, PE, arterial thromboembolic disease (e.g., stroke, MI) disease, or a history of these conditions (See CONTRAINDICATIONS). Immediately discontinue PROMETRIUM if a PE, DVT, stroke, or MI occurs or is suspected.

If feasible, discontinue PROMETRIUM at least 4 to 6 weeks before surgery of the type associated with an increased risk of thromboembolism, or during periods of prolonged immobilization.

The safety and efficacy of estrogen plus progestogen for the prevention of cardiovascular disorders has not been established. (See CLINICAL STUDIES)

The Women’s Health Initiative (WHI) estrogen plus progestin trial reported increased risks of PE, DVT, stroke, and MI in postmenopausal women (50 to 79 years of age, average age 63.4 years) during 5.6 years of treatment with daily oral conjugated estrogens (CE) [0.625 mg] combined with medroxyprogesterone acetate (MPA) [2.5 mg], relative to placebo. Analyses were also conducted in women aged 50-59 years, a group of women more likely to present with new onset of moderate to severe VMS compared to women in other age groups in the trial. (See CLINICAL STUDIES.)

Only daily oral 0.625 mg CE and 2.5 mg MPA were studied in the estrogen plus progestin trial of the WHI. Therefore, the relevance of the WHI findings regarding adverse cardiovascular events to lower CE plus other MPA doses, other routes of administration, or other estrogen plus progestogen products is not known. Without such data, it is not possible to definitively exclude these risks or determine the extent of these risks for other products.

a. Venous Thromboembolism

In women aged 50 to 59 years, the WHI estrogen plus progestin trial reported a relative risk for PE of 2.05 (95% confidence interval [CI], 0.89, 4.71) for CE/MPA compared to placebo, with a risk difference of 6 per 10,000 women-years (WYs; 11 versus 5). The relative risk for DVT was 3.01 (95% CI, 1.36, 6.66) in those receiving CE/MPA compared to placebo, with a risk difference of 10 per 10,000 WYs (15 versus 5). (See CLINICAL STUDIES).

In the overall study population of women aged 50 to 79 years (average 63.4 years), the trial reported a relative risk for PE of 1.98 (95% CI, 1.36, 2.87) for CE/MPA compared to placebo, with a risk difference of 9 per 10,000 WYs (18 versus 9). The relative risk for DVT was 1.87 (95% CI, 1.37, 2.54) for CE/MPA compared to placebo, with a risk difference of 12 per 10,000 WYs (25 versus 14). (See CLINICAL STUDIES).

b. Stroke

In women aged 50 to 59 years, the WHI estrogen plus progestin trial reported a relative risk for stroke of 1.51 (95% CI, 0.81, 2.82) for CE/MPA compared to placebo, with a risk difference of 5 per 10,000 WYs (15 versus 10). (See CLINICAL STUDIES).

In the overall study population of women aged 50 to 79 years (average 63.4 years), the WHI estrogen plus progestin trial reported relative risk for stroke of 1.37 (95% CI, 1.07, 1.76) for CE/MPA compared to placebo, with a risk difference of 9 per 10,000 WYs (33 versus 24). (See CLINICAL STUDIES).

c. Coronary Heart Disease

In women 50 to 59 years of age,the WHI estrogen plus progestin trial reported a relative risk for coronary heart disease (CHD) events (defined as nonfatal MI, silent MI, or CHD death) of 1.34 (95% CI, 0.82, 2.19) for CE/MPA compared placebo, with a risk difference of 5 per 10,000 WYs (23 versus 17).

In the overall study population of women aged 50 to 79 years (average 63.4 years), the trial reported a relative risk of CHD of 1.18 (95% CI, 0.95, 1.45) for CE/MPA compared to placebo, with a risk difference of 6 per 10,000 WYs (41 versus 35). (See CLINICAL STUDIES).

In the Heart and Estrogen/Progestin Replacement Study (HERS) and open label extension (HERS II), postmenopausal women with documented heart disease (n = 2,763, average age 66.7 years) received daily CE (0.625 mg) plus MPA or placebo. In Year 1, there were more CHD events in the CE plus MPA-treated group than placebo; however, rates of CHD events were comparable among both groups for the remainder of the duration of the studies (average total follow-up of 6.8 years).

2. Malignant neoplasms

a. Breast Cancer

Prometrium is contraindicated in women with breast cancer, a history of breast cancer, or estrogen-dependent neoplasia. (See CONTRAINDICATIONS).

Discontinue Prometrium if a hormone-sensitive malignancy is diagnosed. The use of estrogen plus progestin therapy has been reported to result in an increase in abnormal mammograms requiring further evaluation.

Only daily oral CE 0.625 mg and MPA 2.5 mg were studied in the estrogen-alone trial of the WHI. Therefore, the relevance of the WHI findings regarding breast cancer to lower CE plus other MPA doses, other routes of administration, or other estrogen plus progestogen products is not known. Without such data, it is not possible to definitively exclude these risks or determine the extent of these risks for other products.

In women 50-59 years of age, the WHI estrogen plus progestin trial reported a relative risk for invasive breast cancer of 1.21 (95% CI, 0.81, 1.80) for CE/MPA compared to placebo, with a risk difference of 6 per 10,000 WYs (33 versus 27). In this age group, among those who reported no prior use of hormone therapy, the relative risk was 1.06 (95% CI, 0.67, 1.67) for CE/MPA compared to placebo, with a risk difference of 2 per 10,000 WYs (33 versus 31).

In the overall study population of women aged 50-79 years (average 63.4 years), the WHI estrogen plus progestin trial reported a relative risk for invasive breast cancer of 1.24 (95% CI, 1.01, 1.53) for CE/MPA compared to placebo, with a risk difference of 9 per 10,000 WYs (43 versus 35). In the overall study population, among women who reported prior use of hormone therapy, the relative risk of invasive breast cancer was 1.85, (95% CI 1.18, 2.90) for CE/MPA compared to placebo, with a risk difference of 21 per 10,000 WYs (46 versus 25). Among women who reported no prior use of hormone therapy, the relative risk of invasive breast cancer was 1.09, (95% CI 0.86, 1.39), with a risk difference of 4 per 10,000 WYs (40 versus 36). Invasive breast cancers were larger, were more likely to be node positive, and were diagnosed at a more advanced stage in the CE/MPA group compared with the placebo group. Metastatic disease was rare, with no apparent difference between the two groups. Other prognostic factors such as histologic subtype, grade and hormone receptor status did not differ between the groups. (See CLINICAL STUDIES.) Extension of the WHI trial also demonstrated increased breast cancer risk associated with estrogen plus progestin therapy.

Consistent with the WHI trial, observational studies have also reported an increased risk of breast cancer with estrogen plus progestin therapy. A large meta-analysis including 24 prospective studies of postmenopausal women comparing current use of estrogen plus progestin products with use duration of 5 to 14 years (average of 9 years) versus never use reported a relative risk for breast cancer of 2.08 (95% CI, 2.02 to 2.15). These studies have not generally found significant variation in the risk of breast cancer among different estrogen plus progestin combinations, doses, or routes of administration.

Regarding breast cancer mortality, the WHI estrogen plus progestin trial did not show a statistically significant difference between CE/MPA and placebo. The trial reported a relative risk of 1.35 (95% CI, 0.94 to 1.95) for CE/MPA compared to placebo, with a risk difference of 1 per 10,000 WYs (5 versus 4) after a median of 19 years of cumulative follow-up.

b. Ovarian Cancer

In the overall WHI study population of women aged 50 to 79 years (average 63.4 years), the estrogen plus progestin trial reported a relative risk for ovarian cancer of 1.41 (95% CI, 0.75 to 2.66) for CE/MPA versus placebo after an average follow-up of 5.6 years. The risk difference was 1 per 10,000 WYs (5 versus 4). Comparing CE/MPA to placebo, women 50 to 59 years of age had a relative risk for ovarian cancer of 0.30 (95% CI 0.06, 1.47) and the risk difference was -3 per 10,000 WYs (1 versus 4).

A large meta-analysis including 17 prospective studies of postmenopausal women compared current use of estrogen plus progestin products versus never use and reported a relative risk for ovarian cancer of 1.37 (95% CI, 1.26 to 1.48). The duration of hormone therapy use that was associated with an increased risk of ovarian cancer is unknown.

3. Vision abnormalities

Retinal vascular thrombosis has been reported in patients receiving estrogen. Discontinue estrogen plus progestin therapy pending examination if there is sudden partial or complete loss of vision, or if there is a sudden onset of proptosis, diplopia or migraine. If examination reveals papilledema or retinal vascular lesions, estrogen plus progestin therapy should be permanently discontinued.

PRECAUTIONS

A. General

1. Fluid Retention

Progesterone may cause some degree of fluid retention. Women with conditions that might be influenced by this factor, such as cardiac or renal dysfunction, warrant careful observation.

2. Dizziness and Drowsiness

PROMETRIUM® (progesterone, USP) Capsules may cause transient dizziness and drowsiness and should be used with caution when driving a motor vehicle or operating machinery. PROMETRIUM Capsules should be taken as a single daily dose at bedtime.

B. Patient Information

General: This product contains peanut oil and should not be used if you are allergic to peanuts.

Physicians are advised to discuss the contents of the Patient Information leaflet with patients for whom they prescribe PROMETRIUM Capsules.

C. Drug-Laboratory Test Interactions

The following laboratory results may be altered by the use of estrogen plus progestin therapy:

- Increased sulfobromophthalein retention and other hepatic function tests.
- Coagulation tests: increase in prothrombin factors VII, VIII, IX and X.
- Pregnanediol determination.
- Thyroid function: increase in PBI, and butanol extractable protein bound iodine and decrease in T3 uptake values.

D. Carcinogenesis, Mutagenesis, Impairment of Fertility

Progesterone has not been tested for carcinogenicity in animals by the oral route of administration. When implanted into female mice, progesterone produced mammary carcinomas, ovarian granulosa cell tumors and endometrial stromal sarcomas. In dogs, long-term intramuscular injections produced nodular hyperplasia and benign and malignant mammary tumors. Subcutaneous or intramuscular injections of progesterone decreased the latency period and increased the incidence of mammary tumors in rats previously treated with a chemical carcinogen.

Progesterone did not show evidence of genotoxicity in in vitro studies for point mutations or for chromosomal damage. In vivo studies for chromosome damage have yielded positive results in mice at oral doses of 1000 mg/kg and 2000 mg/kg. Exogenously administered progesterone has been shown to inhibit ovulation in a number of species and it is expected that high doses given for an extended duration would impair fertility until the cessation of treatment.

E. Pregnancy

PROMETRIUM Capsules should not be used during pregnancy.

Pregnancy Category B: Reproductive studies have been performed in mice at doses up to 9 times the human oral dose, in rats at doses up to 44 times the human oral dose, in rabbits at a dose of 10 mcg/day delivered locally within the uterus by an implanted device, in guinea pigs at doses of approximately one-half the human oral dose and in rhesus monkeys at doses approximately the human dose, all based on body surface area, and have revealed little or no evidence of impaired fertility or harm to the fetus due to progesterone.

F. Nursing Women

Detectable amounts of progestin have been identified in the milk of nursing women receiving progestins. Caution should be exercised when PROMETRIUM Capsules are administered to a nursing woman.

G. Pediatric Use

PROMETRIUM Capsules are not indicated in children. Clinical studies have not been conducted in the pediatric population.

H. Geriatric Use

There have not been sufficient numbers of geriatric women involved in clinical studies utilizing PROMETRIUM Capsules to determine whether those over 65 years of age differ from younger subjects in their response to PROMETRIUM Capsules.

The Women's Health Initiative Study

In the Women's Health Initiative (WHI) estrogen plus progestin substudy (daily CE [0.625 mg] plus MPA [2.5 mg] versus placebo), there was a higher relative risk of nonfatal stroke and invasive breast cancer in women greater than 65 years of age. (See CLINICAL STUDIES and WARNINGS, Cardiovascular disorders and Malignant neoplasms.)

The Women's Health Initiative Memory Study

In the Women's Health Initiative Memory Study (WHIMS) of postmenopausal women 65 to 79 years of age, there was an increased risk of developing probable dementia in the estrogen plus progestin ancillary study when compared to placebo. (See CLINICAL STUDIES.)

ADVERSE REACTIONS

See WARNINGS and PRECAUTIONS.

Because clinical trials are conducted under widely varying conditions, adverse reaction rates observed in the clinical trials of a drug cannot be directly compared to rates in the clinical trials of another drug and may not reflect the rates observed in practice.

In a multicenter, randomized, double-blind, placebo-controlled clinical trial, the effects of PROMETRIUM Capsules on the endometrium was studied in a total of 875 postmenopausal women. Table 7 lists adverse reactions greater than or equal to 2 percent of women who received cyclic PROMETRIUM Capsules 200 mg daily (12 days per calendar month cycle) with 0.625 mg conjugated estrogens or placebo.

TABLE 7. Adverse Reactions (≥ 2%) Reported in an 875 Patient Placebo-Controlled Trial in Postmenopausal Women Over a 3-Year Period [Percentage (%) of Patients Reporting]
 | PROMETRIUM Capsules 200 mg with Conjugated Estrogens 0.625 mg | Placebo
 | (n=178) | (n=174)
Headache | 31 | 27
Breast Tenderness | 27 | 6
Joint Pain | 20 | 29
Depression | 19 | 12
Dizziness | 15 | 9
Abdominal Bloating | 12 | 5
Hot Flashes | 11 | 35
Urinary Problems | 11 | 9
Abdominal Pain | 10 | 10
Vaginal Discharge | 10 | 3
Nausea / Vomiting | 8 | 7
Worry | 8 | 4
Chest Pain | 7 | 5
Diarrhea | 7 | 4
Night Sweats | 7 | 17
Breast Pain | 6 | 2
Swelling of Hands and Feet | 6 | 9
Vaginal Dryness | 6 | 10
Constipation | 3 | 2
Breast Carcinoma | 2 | <1
Breast Excisional Biopsy | 2 | <1
Cholecystectomy | 2 | <1

Effects on Secondary Amenorrhea

In a multicenter, randomized, double-blind, placebo-controlled clinical trial, the effects of PROMETRIUM® (progesterone, USP) Capsules on secondary amenorrhea was studied in 49 estrogen-primed postmenopausal women. Table 8 lists adverse reactions greater than or equal to 5 percent of women who received PROMETRIUM Capsules or placebo.

TABLE 8. Adverse Reactions (≥ 5%) Reported in Patients Using 400 mg/day in a Placebo-Controlled Trial in Estrogen-Primed Postmenopausal Women
Adverse Experience | PROMETRIUM Capsules 400 mg | Placebo
 | n=25 | n=24
 | Percentage (%) of Patients
Fatigue | 8 | 4
Headache | 16 | 8
Dizziness | 24 | 4
Abdominal Distention (Bloating) | 8 | 8
Abdominal Pain (Cramping) | 20 | 13
Diarrhea | 8 | 4
Nausea | 8 | 0
Back Pain | 8 | 8
Musculoskeletal Pain | 12 | 4
Irritability | 8 | 4
Breast Pain | 16 | 8
Infection Viral | 12 | 0
Coughing | 8 | 0

In a multicenter, parallel-group, open label postmarketing dosing study consisting of three consecutive 28-day treatment cycles, 220 premenopausal women with secondary amenorrhea were randomized to receive daily conjugated estrogens therapy (0.625 mg conjugated estrogens) and PROMETRIUM Capsules, 300 mg per day (n=113) or PROMETRIUM Capsules, 400 mg per /day (n=107) for 10 days of each treatment cycle. Overall, the most frequently reported treatment-emergent adverse reactions, reported in greater than or equal to 5 percent of subjects, were nausea, fatigue, vaginal mycosis, nasopharyngitis, upper respiratory tract infection, headache, dizziness, breast tenderness, abdominal distension, acne, dysmenorrhea, mood swing, and urinary tract infection.

Postmarketing Experience:

The following additional adverse reactions have been reported with PROMETRIUM Capsules. Because these reactions are reported voluntarily from a population of uncertain size, it is not always possible to reliably estimate the frequency or establish a causal relationship to drug exposure.

Genitourinary System: endometrial carcinoma, hypospadia, intra-uterine death, menorrhagia, menstrual disorder, metrorrhagia, ovarian cyst, spontaneous abortion.

Cardiovascular: circulatory collapse, congenital heart disease (including ventricular septal defect and patent ductus arteriosus), hypertension, hypotension, tachycardia.

Gastrointestinal: acute pancreatitis, cholestasis, cholestatic hepatitis, dysphagia, hepatic failure, hepatic necrosis, hepatitis, increased liver function tests (including alanine aminotransferase increased, aspartate aminotransferase increased, gamma-glutamyl transferase increased), jaundice, swollen tongue.

Skin: alopecia, pruritus, urticaria.

Eyes: blurred vision, diplopia, visual disturbance.

Central Nervous System: aggression, convulsion, depersonalization, depressed consciousness, disorientation, dysarthria, loss of consciousness, paresthesia, sedation, stupor, syncope (with and without hypotension), transient ischemic attack, suicidal ideation.

During initial therapy, a few women have experienced a constellation of many or all of the following symptoms: extreme dizziness and/or drowsiness, blurred vision, slurred speech, difficulty walking, loss of consciousness, vertigo, confusion, disorientation, feeling drunk, and shortness of breath.

Miscellaneous: abnormal gait, anaphylactic reaction, arthralgia, blood glucose increased, choking, cleft lip, cleft palate, difficulty walking, dyspnea, face edema, feeling abnormal, feeling drunk, hypersensitivity, asthma, muscle cramp, throat tightness, tinnitus, vertigo, weight decreased, weight increased.

OVERDOSAGE

No studies on overdosage have been conducted in humans. In the case of overdosage, PROMETRIUM® (progesterone, USP) Capsules should be discontinued and the patient should be treated symptomatically.

DOSAGE AND ADMINISTRATION

Prevention of Endometrial Hyperplasia

PROMETRIUM Capsules should be given as a single daily dose at bedtime, 200 mg orally for 12 days sequentially per 28-day cycle, to a postmenopausal woman with a uterus who is receiving daily conjugated estrogens tablets.

Treatment of Secondary Amenorrhea

PROMETRIUM Capsules may be given as a single daily dose of 400 mg at bedtime for 10 days.

Some women may experience difficulty swallowing PROMETRIUM Capsules. For these women, PROMETRIUM Capsules should be taken with a glass of water while in the standing position.

HOW SUPPLIED

PROMETRIUM® (progesterone, USP) Capsules 100 mg are round, peach-colored capsules branded with black imprint "SV."

NDC 72989-372-30 (Bottle of 30)

PROMETRIUM® (progesterone, USP) Capsules 200 mg are oval, pale yellow-colored capsules branded with black imprint "SV2."

NDC 72989-373-30 (Bottle of 30)

STORAGE AND HANDLING

Store at 25°C (77°F); excursions permitted to 15° to 30°C (59° to 86°F) [See USP Controlled Room Temperature].
Protect from excessive moisture.
Dispense in tight, light-resistant container as defined in USP/NF, accompanied by a Patient Insert.
Keep out of reach of children.

Distributed by:
Acertis Pharmaceuticals, LLC
Raleigh, NC 27601
1-888-848-3593

10225 Rev. 02/2026

PATIENT INFORMATION

PROMETRIUM® (progesterone, USP)

Capsules 100 mg
Capsules 200 mg

Rx only

Read this PATIENT INFORMATION before you start taking PROMETRIUM® (progesterone, USP) Capsules and read what you get each time you refill your PROMETRIUM Capsules prescription. There may be new information. This information does not take the place of talking to your healthcare provider about your medical condition or your treatment.

THIS PRODUCT CONTAINS PEANUT OIL AND SHOULD NOT BE USED IF YOU ARE ALLERGIC TO PEANUTS.

What is PROMETRIUM Capsules?

PROMETRIUM Capsules contain the female hormone called progesterone.

What is PROMETRIUM Capsules used for?

Treatment of Menstrual Irregularities

PROMETRIUM Capsules are used for the treatment of secondary amenorrhea (absence of menstrual periods in women who have previously had a menstrual period) due to a decrease in progesterone. When you do not produce enough progesterone, menstrual irregularities can occur. If your healthcare provider has determined your body does not produce enough progesterone on its own, PROMETRIUM Capsules may be prescribed to provide the progesterone you need.

Protection of the Endometrium (Lining of the Uterus)

PROMETRIUM Capsules are used in combination with estrogen-containing medications in a postmenopausal woman with a uterus (womb). Taking estrogen-alone increases the chance of developing a condition called endometrial hyperplasia that may lead to cancer of the lining of the uterus (womb). The addition of a progestin is generally recommended for a woman with a uterus to reduce the chance of getting cancer of the uterus (womb).

Who should not take PROMETRIUM Capsules?

Do not start taking PROMETRIUM Capsules if you:

- Are allergic to peanuts
- Have unusual vaginal bleeding
- Currently have or have had certain cancers
  Estrogen plus progestin treatment may increase the chance of getting certain types of cancers, including cancer of the breast or uterus. If you have or have had cancer, talk with your healthcare provider about whether you should take PROMETRIUM Capsules.
- Had a stroke or heart attack
- Currently have or have had blood clots
- Currently have or have had liver problems
- Are allergic to PROMETRIUM Capsules or any of its ingredients
  See the list of ingredients in PROMETRIUM Capsules at the end of this leaflet.

Tell your healthcare provider:

- If you are breastfeeding. The hormone in PROMETRIUM Capsules can pass into your breast milk.
- About all of your medical problems. Your healthcare provider may need to check you more carefully if you have certain conditions, such as asthma (wheezing), epilepsy (seizures), diabetes, migraine, endometriosis, lupus, problems with your heart, liver, thyroid, or kidneys, or have high calcium levels in your blood.
- About all the medicines you take. This includes prescription and nonprescription medicines, vitamins, and herbal supplements. Some medicines may affect how PROMETRIUM Capsules work. PROMETRIUM Capsules may also affect how your other medicines work.

How should I take PROMETRIUM Capsules?

1. Prevention of Endometrial Hyperplasia: A post-menopausal woman with a uterus who is taking estrogens should take a single daily dose of 200 mg PROMETRIUM Capsules at bedtime for 12 continuous days per 28-day cycle.
2. Secondary Amenorrhea: PROMETRIUM Capsules may be given as a single daily dose of 400 mg at bedtime for 10 days.
3. PROMETRIUM Capsules are to be taken at bedtime as some women become very drowsy and/or dizzy after taking PROMETRIUM Capsules. In a few cases, symptoms may include blurred vision, difficulty speaking, difficulty with walking, and feeling abnormal. If you experience these symptoms, discuss them with your healthcare provider right away.
4. If you experience difficulty in swallowing PROMETRIUM Capsules, it is recommended that you take your daily dose at bedtime with a glass of water while in the standing position.

What are the possible side effects of PROMETRIUM Capsules?

Side effects are grouped by how serious they are and how often they happen when you are treated:

Serious, but less common side effects include:

- Risk to the Fetus: Cases of cleft palate, cleft lip, hypospadias, ventricular septal defect, patent ductus arteriosus, and other congenital heart defects.
- Abnormal Blood Clotting: Stroke, heart attack, pulmonary embolus, visual loss or blindness.

Some of the warning signs of serious side effects include:

- Changes in vision or speech
- Sudden new severe headaches
- Severe pains in your chest or legs with or without shortness of breath, weakness and fatigue
- Dizziness and faintness
- Vomiting

Call your healthcare provider right away if you get any of these warning signs, or any other unusual symptoms that concern you.

Less serious, but common side effects include:

- Headaches
- Breast pain
- Irregular vaginal bleeding or spotting
- Stomach or abdominal cramps, bloating
- Nausea and vomiting
- Hair loss
- Fluid retention
- Vaginal yeast infection

These are not all the possible side effects of PROMETRIUM® (progesterone, USP) Capsules. For more information, ask your healthcare provider or pharmacist for advice about side effects. You may report side effects to Acertis Pharmaceuticals, LLC at 1-888-848-3593 or to FDA at 1-800-FDA-1088.

What can I do to lower my chances of getting a serious side effect with PROMETRIUM Capsules?

- Talk with your healthcare provider regularly about whether you should continue taking PROMETRIUM Capsules.
- See your healthcare provider right away if you get unusual vaginal bleeding while taking PROMETRIUM Capsules.
- Have a pelvic exam, breast exam, and mammogram (breast X-ray) every year unless your healthcare provider tells you something else. If members of your family have had breast cancer or if you have ever had breast lumps or an abnormal mammogram, you may need to have breast exams more often.
- If you have high blood pressure, high cholesterol (fat in the blood), diabetes, are overweight, or if you use tobacco, you may have higher chances for getting heart disease. Ask your healthcare provider for ways to lower your chances for getting heart disease.

General information about safe and effective use of PROMETRIUM Capsules

- Medicines are sometimes prescribed for conditions that are not mentioned in patient information leaflets. Do not take PROMETRIUM Capsules for conditions for which it was not prescribed.
- Your healthcare provider has prescribed this drug for you and you alone. Do not give PROMETRIUM Capsules to other people, even if they have the same symptoms you have. It may harm them.
- PROMETRIUM Capsules should be taken as a single daily dose at bedtime. Some women may experience extreme dizziness and/or drowsiness during initial therapy. In a few cases, symptoms may include blurred vision, difficulty speaking, difficulty with walking, and feeling abnormal. If you experience these symptoms, discuss them with your healthcare provider right away.
- Use caution when driving a motor vehicle or operating machinery as dizziness or drowsiness may occur.

Keep PROMETRIUM Capsules out of the reach of children.

This leaflet provides a summary of the most important information about PROMETRIUM Capsules. If you would like more information, talk with your healthcare provider or pharmacist. You can ask for information about PROMETRIUM Capsules that is written for health professionals. You can get more information by calling the toll free number 1-888-848-3593.

What are the ingredients in PROMETRIUM Capsules?

Active ingredient: 100 mg or 200 mg micronized progesterone

The inactive ingredients for PROMETRIUM Capsules 100 mg include: peanut oil NF, gelatin NF, glycerin USP, lecithin NF, titanium dioxide USP, FD&C Red No. 40, and D&C Yellow No. 10.

The inactive ingredients for PROMETRIUM Capsules 200 mg include: peanut oil NF, gelatin NF, glycerin USP, lecithin NF, titanium dioxide USP, D&C Yellow No. 10, and FD&C Yellow No. 6.

HOW SUPPLIED

PROMETRIUM Capsules 100 mg are round, peach-colored capsules branded with black imprint "SV."

PROMETRIUM Capsules 200 mg are oval, pale yellow-colored capsules branded with black imprint "SV2."

Store at 25°C (77°F); excursions permitted to 15° to 30°C (59° to 86°F) [See USP Controlled Room Temperature].

Protect from excessive moisture.

Distributed by:
Acertis Pharmaceuticals, LLC
Raleigh, NC 276011-888-848-3593

10226 Rev. 02/2026

PRINCIPAL DISPLAY PANEL - 100 mg Capsule Bottle Label

30 Capsules
NDC 72989-372-30

PROMETRIUM®
(progesterone, USP)
Capsules

SV 100 mg

Rx only

DO NOT USE IF ALLERGIC TO PEANUTS

acertis TM
PHARMACEUTICALS

PRINCIPAL DISPLAY PANEL - 200 mg Capsule Bottle Label

30 Capsules
NDC 72989-373-30

PROMETRIUM®
(progesterone, USP)
Capsules

SV2 200 mg

Rx only

DO NOT USE IF ALLERGIC
TO PEANUTS

acertis TM
PHARMACEUTICALS